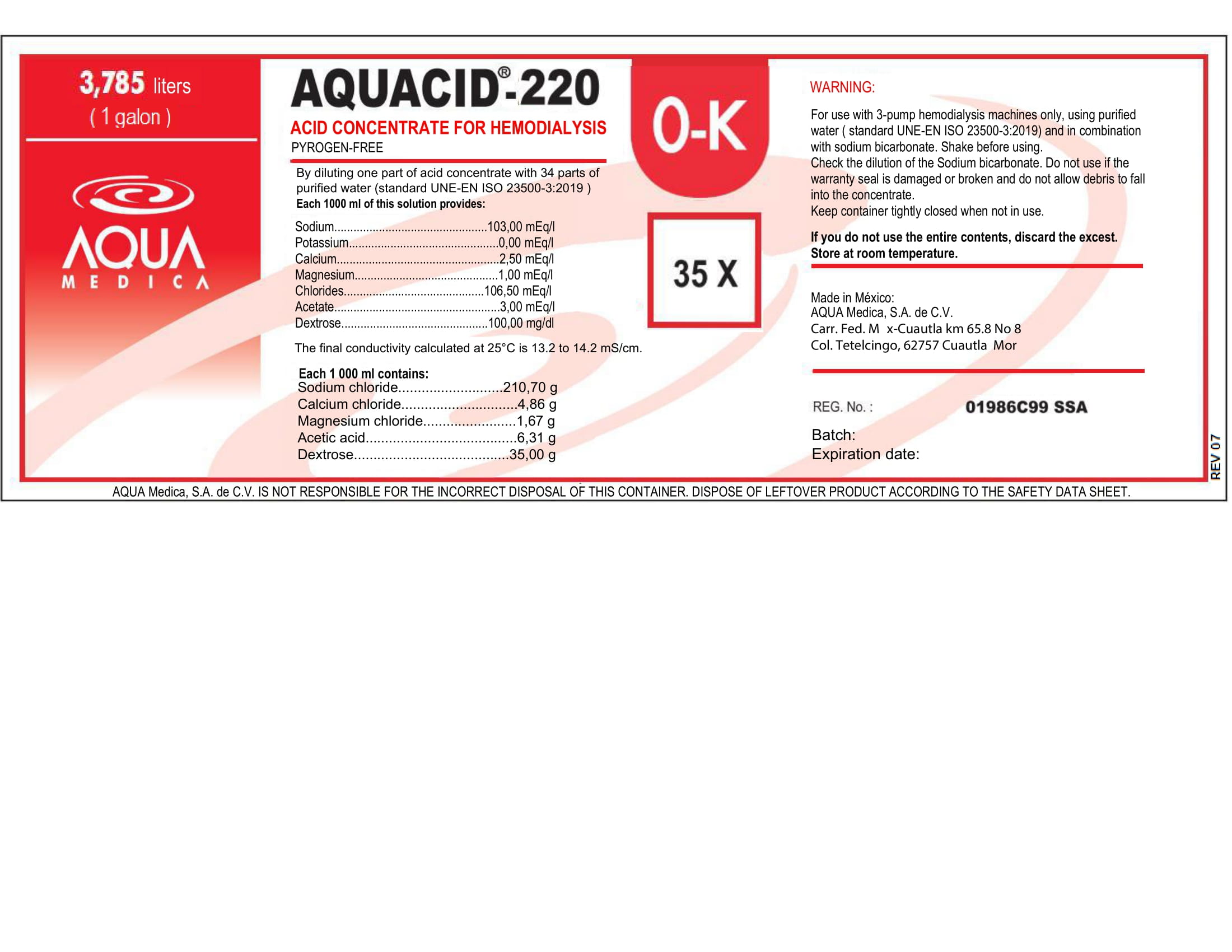 DRUG LABEL: AQUACID-220
NDC: 81943-602 | Form: SOLUTION, CONCENTRATE
Manufacturer: Aqua Medica, S.A. de C.V.
Category: otc | Type: HUMAN OTC DRUG LABEL
Date: 20251110

ACTIVE INGREDIENTS: POTASSIUM CHLORATE 0.671 g/100 mL
INACTIVE INGREDIENTS: SODIUM CHLORIDE 21.07 g/100 mL; MAGNESIUM CHLORIDE 0.167 g/100 mL; CALCIUM CHLORIDE 0.486 g/100 mL; ACETIC ACID C-11 0.631 g/100 mL; DEXTROSE 3.5 g/100 mL; WATER

This is a Hemodialysis Acid Concentrate, Pyrogen-Free.

By diluiting one part of this acid concentrate with 34 parts of purified water (ISO Standard 13959:2014), each 1000 ml of this solucion provides:

Sodium: 103.00 mEq/l

Potassium: 0.00 mEq/l

Calcium: 2.50 mEq/l

Magnesium: 1.00 mEq/l

Chlorides: 106.50 mEq/l

Acetate: 3.00 mEq/l

Dextrose: 100.00 mEq/l

The final conductivity calculated at 25 C is 13.2 to 14.2 mS/cm.

Active Ingredient(s)

Potassium Chloride

Purpose

For use with 3-pump hemodialysis machines only.

Use

For use with 3-pump hemodialysis machines only, using purified water (Standard 13959:2014) and in combination with sodium bicarbonate.

Warnings

For use with 3-pump hemodialysis machines only.

Do not use

- If the warranty seal is damaged or broken and do not allow debris to fall into the concentrate.

WHEN USING

Using purified water (Standard 13959:2014) and in combination with sodium bicarbonate.
Keep out of reach of children. If swallowed, get medical help or contact a Poison Control Center right away.

STOP USE

If you do not use the entire contents, discard the excess.

Keep out of reach of children. If swallowed, get medical help or contact a Poison Control Center right away.

Directions

- By diluting one part of this acid concentrate with 34 parts of purified water (ISO Standard 13959:2014).

Other information

- Store at room temperature.
- If you do not use the entire contents, discard the excess.

Inactive ingredients

Sodium chloride, calcium chloride, magnesium chloride, acetic acid, dextrose, purified water USP

RECENT MAJOR CHANGES

For use with 3-pump hemodialysis machines only, using purified water (Standard 13959:2014) and in combination with sodium bicarbonate.

By diluting one part of this acid concentrate with 34 parts of purified water (ISO Standard 13959:2014).

Package Label - Principal Display Panel

3785 mL NDC: 81943-602-04